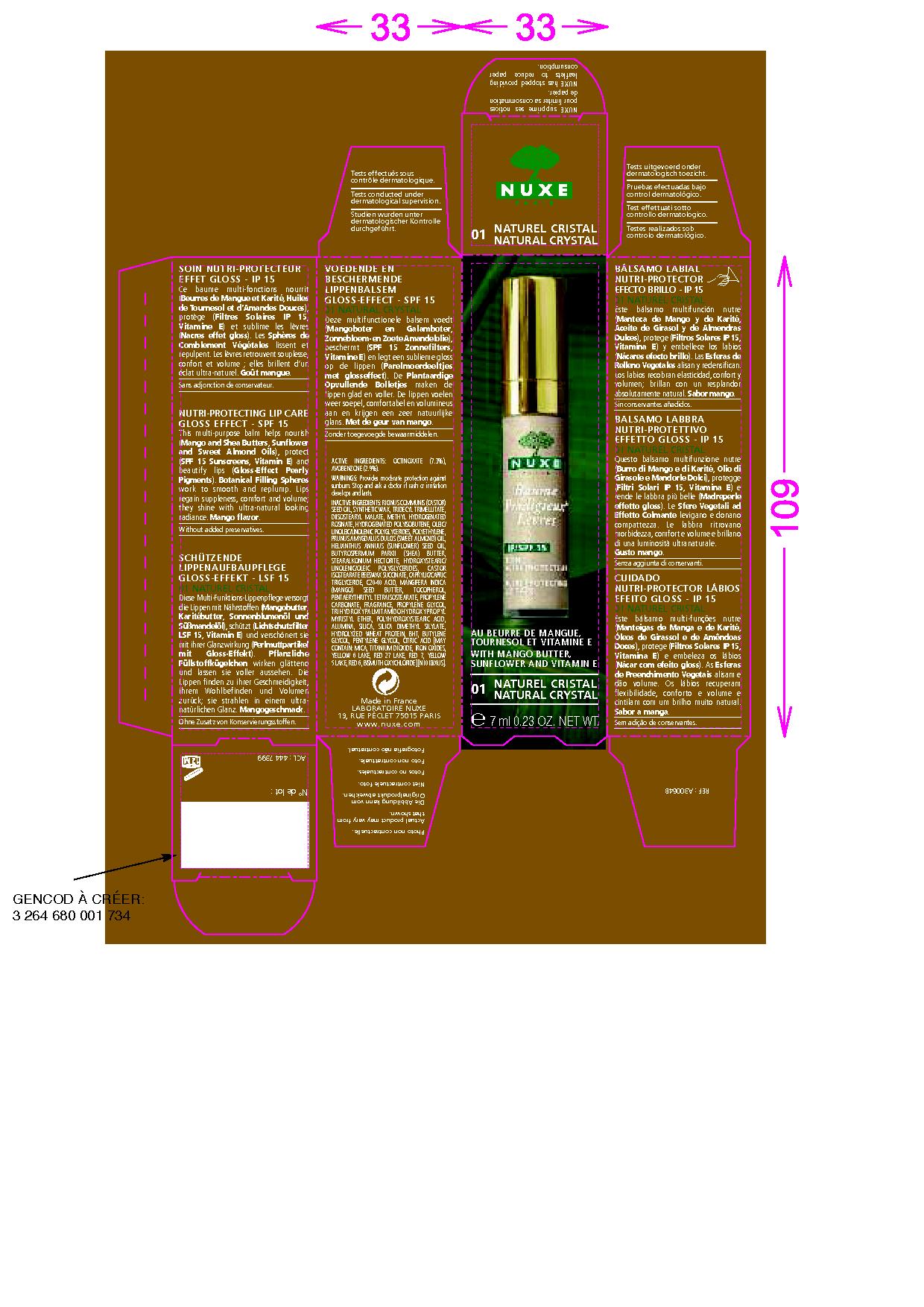 DRUG LABEL: BAUME PRODIGIEUX LEVRES 01 NATURAL CRYSTAL
NDC: 67542-010 | Form: LIPSTICK
Manufacturer: LABORATOIRE NUXE
Category: otc | Type: HUMAN OTC DRUG LABEL
Date: 20091201

ACTIVE INGREDIENTS: OCTINOXATE 7.3 mL/100 mL; AVOBENZONE 2.9 mL/100 mL
INACTIVE INGREDIENTS: CASTOR OIL; DIISOSTEARYL MALATE; TRIDECYL TRIMELLITATE; HIGH DENSITY POLYETHYLENE; ALMOND OIL; SUNFLOWER OIL; SHEA BUTTER; TITANIUM DIOXIDE; MEDIUM-CHAIN TRIGLYCERIDES; MANGIFERA INDICA SEED BUTTER; MICA; TOCOPHEROL; PENTAERYTHRITYL TETRAISOSTEARATE; PROPYLENE CARBONATE; TRIHYDROXYPALMITAMIDOHYDROXYPROPYL MYRISTYL ETHER; FERRIC OXIDE RED; POLYHYDROXYSTEARIC ACID (2300 MW); C20-40 ACID; HYDROGENATED POLYBUTENE (1300 MW); SYNTHETIC WAX (1200 MW)

Drug Facts

PURPOSE

.

PACKAGE LABEL

ACTIVE INGREDIENTS : OCTINOXATE (7.3%), AVOBENZONE (2.9%)
WARNINGS : Provides moderate protection against sunburn. Stop and ask a doctor if rash or irritation develops and lasts.